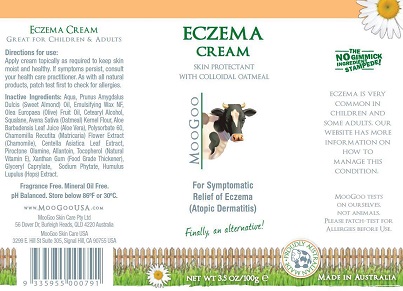 DRUG LABEL: Eczema
NDC: 69788-001 | Form: CREAM
Manufacturer: MooGoo USA LLC
Category: otc | Type: HUMAN OTC DRUG LABEL
Date: 20160405

ACTIVE INGREDIENTS: OATMEAL 2.5 g/100 g
INACTIVE INGREDIENTS: WATER; ALMOND OIL; CETOSTEARYL ALCOHOL; POLYSORBATE 60; PEG-150 STEARATE; STEARETH-20; OLIVE OIL; SQUALANE; AVENA SATIVA TOP; ALOE VERA LEAF; CHAMOMILE; CENTELLA ASIATICA LEAF; PIROCTONE OLAMINE; ALLANTOIN; TOCOPHEROL; XANTHAN GUM; GLYCERYL CAPRYLATE; PHYTATE SODIUM; HUMULUS LUPULUS WHOLE

Active Ingredient Purpose

Colloidal Oatmeal 2.5% ............. Skin Protectant

Uses

Protects and helps relieve eczema (Atopic Dermatitis)

Keep out of reach of children. If swallowed, get medical help or contact a Poison Control Center immediately.

INDICATIONS AND USAGE

Eczema Cream

Skin Protectant with Colloidal Oatmeal

MooGoo

For Symptomatic Relief of Eczema (Atopic Dermatitis)

Finally, an alternative!

Eczema is very common in children and some adults. Our website has more information on how to manage this condition.

MooGoo products originate from a cream used in australian dairy farms to repair the skin on cow's udders! This cream was full of natural skin healing ingredients, and no gimmicks. All MooGoo products are made this way.

Directions

Apply as needed to affected area. For use on mild to moderate eczema or as directed by a physician.

Warnings

For external use only. When using this product do not get into eyes.

Stop use and ask a doctor if

- condition worsens
- symptoms last more than 7 days or clear up and occur again within a few days

Inactive Ingredients

aqua, prunus amygdalus dulcis (sweet almond) oil, emulsifying wax NF, olea europaea (olive) fruit oil, cetearyl alcohol, squalane, avena sativa (oatmeal) kernel flour, aloe barbadensis leaf juice (aloe vera), polysorbate 60, chamomilla recutita (matricaria) flower extract (chamomile), centella asiatica leaf extract, piroctone olamine, allantoin, tocopherol (natural vitamin E), xanthan gum (food grade thickener), glyceryl caprylate, sodium phytate, humulus lupulus (hops) extract.